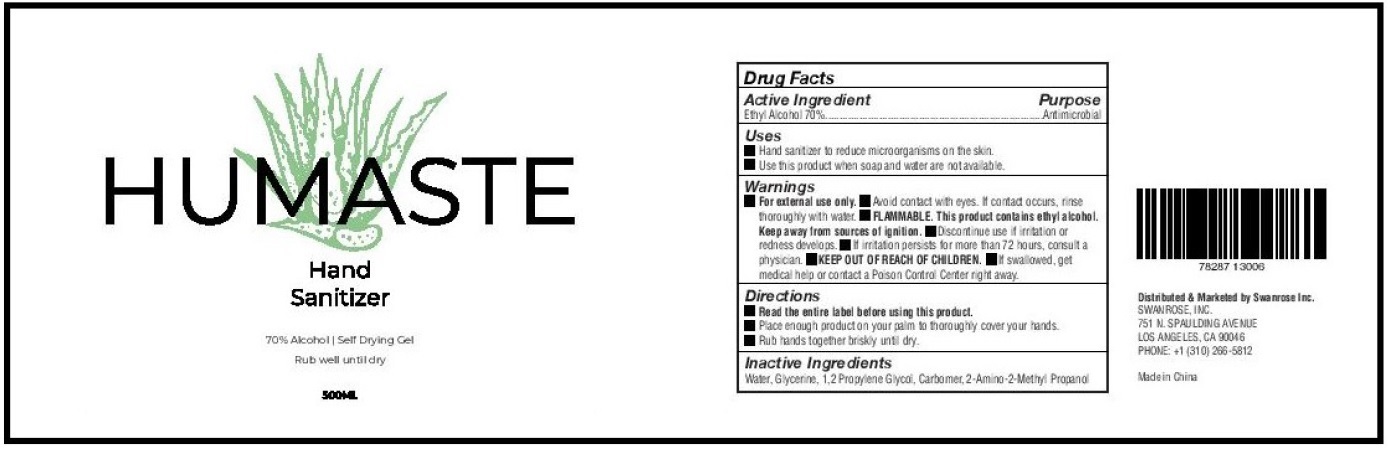 DRUG LABEL: HUMASTE Hand Sanitizer
NDC: 78287-130 | Form: GEL
Manufacturer: Swanrose, Inc.
Category: otc | Type: HUMAN OTC DRUG LABEL
Date: 20200627

ACTIVE INGREDIENTS: ALCOHOL 70 mL/100 mL
INACTIVE INGREDIENTS: WATER; GLYCERIN; PROPYLENE GLYCOL; CARBOMER HOMOPOLYMER, UNSPECIFIED TYPE; AMINOMETHYLPROPANOL

HUMASTE Hand Sanitizer

Active Ingredient

Ethyl Alcohol 70%

Purpose

Antimicrobial

Uses

• Hand sanitizer to reduce microorganisms on the skin.
• Use this product when soap and water are not available.

Warnings

• For external use only. • Avoid contact with eyes. If contact occurs, rinse thoroughly with water. • FLAMMABLE. This product contains ethyl alcohol. Keep away from sources of ignition. • Discontinue use if irritation or redness develops. • If irritation persists for more than 72 hours, consult a physician.

• KEEP OUT OF REACH OF CHILDREN.

• If swallowed, get medical help or contact a Poison Control Center right away.

Directions

• Read the entire label before using this product.
• Place enough product on your palm to thoroughly cover your hands.
• Rub hands together briskly until dry.

Inactive Ingredients

Water, Glycerine, 1,2 Propylene Glycol, Carbomer, 2-Amino-2-Methyl Propanol

70% Alcohol
Self Drying Gel
Rub well until dry

Distributed & Marketed by Swanrose Inc.
SWANROSE, INC.
751 N. SPAULDING AVENUE
LOS ANGELES, CA 90046
PHONE: +1 (310) 266-5812
Made in China